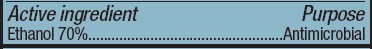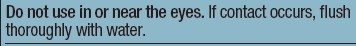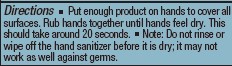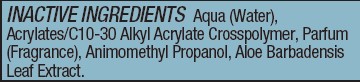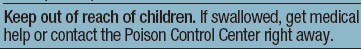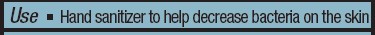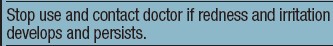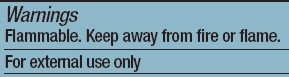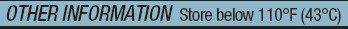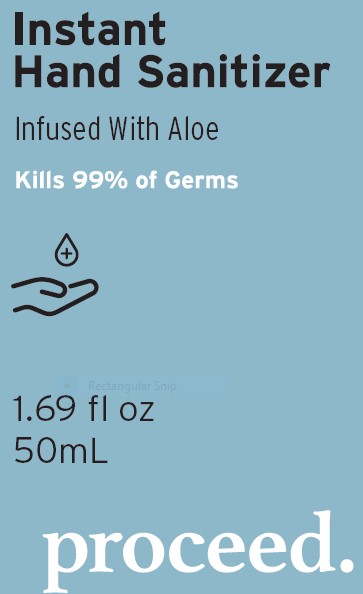 DRUG LABEL: Hand Sanitizer
NDC: 80380-071 | Form: GEL
Manufacturer: Shedrain Corporation
Category: otc | Type: HUMAN OTC DRUG LABEL
Date: 20201023

ACTIVE INGREDIENTS: ALCOHOL 70 mL/100 mL
INACTIVE INGREDIENTS: CARBOMER INTERPOLYMER TYPE A (ALLYL SUCROSE CROSSLINKED) 0.6 mL/100 mL; AMINOMETHYL PROPANEDIOL 0.15 mL/100 mL; WATER; ALOE VERA LEAF 0.1 mL/100 mL

Active Ingredient(s)

Ethanol 70%. Purpose: Antimicrobial

Purpose

Hand sanitizer to help decrease bacteria on the skin.

Warnings

Flammable. Keep away from fire or flame.

For external use only

Do not use in or near the eyes. If contact occurs, flush thoroughly with water.

Stop use and contact doctor if redness and irritation develops and persists.

Keep out of reach of children. If swallowed, get medical help or contact the Poison Control Center right away.

Directions

Put enough product on hands to cover all surfaces. Rub hands together until hands feel dry. This should take around 20 seconds. Note: Do not rinse or wipe off the hand sanitizer before it is dry; it may not work as well against germs.

Other information

Store below 110°F (43°C)

Inactive ingredients

Aqua (Water), Acrylates/C10-30 Alkyl Acrylate Crosspolymer, Parfum (Fragrance), Animomethyl Propanol, Aloe Barbadensis Leaf Extract.

INDICATIONS AND USAGE

Put enough product on hands to cover all surfaces. Rub hands together until hands feel dry. This should take around 20 seconds. Note: Do not rinse or wipe off the hand sanitizer before it is dry; it may not work as well against germs.

Package Label - Principal Display Panel

Instant Hand Sanitizer. 50mL